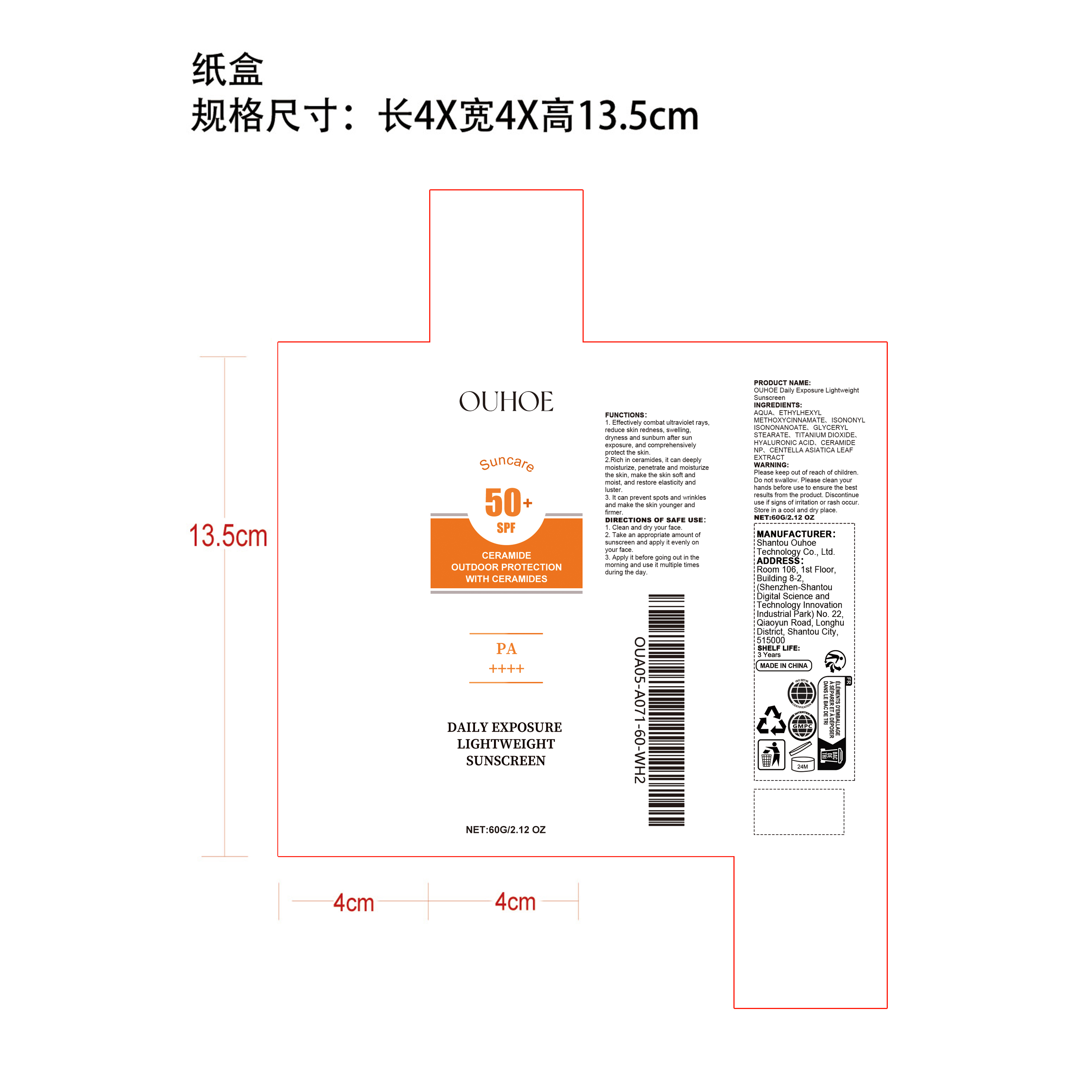 DRUG LABEL: OUHOE Daily Exposure Lightweight Sunscreen
NDC: 85163-013 | Form: CREAM
Manufacturer: Shantou Ouhoe Technology Co., Ltd.
Category: otc | Type: HUMAN OTC DRUG LABEL
Date: 20251206

ACTIVE INGREDIENTS: CENTELLA ASIATICA LEAF 0.012 mg/60 mg
INACTIVE INGREDIENTS: AQUA 53.064 mg/60 mg; HYALURONIC ACID 0.012 mg/60 mg; TITANIUM DIOXIDE 0.6 mg/60 mg; ETHYLHEXYL METHOXYCINNAMATE 3 mg/60 mg; CERAMIDE NP 0.012 mg/60 mg; GLYCERYL STEARATE 0.9 mg/60 mg; ISONONYL ISONONANOATE 2.4 mg/60 mg

ACTIVE INGREDIENT

CENTELLA ASIATICA LEAF EXTRACT

PURPOSE

1. Effectively combat ultraviolet rays, reduce skin redness, swelling, dryness and sunburn after sun exposure, and comprehensively protect the skin.

2.Rich in ceramides, it can deeply moisturize, penetrate and moisturize the skin, make the skin soft and moist, and restore elasticity and luster.

3. It can prevent spots and wrinkles and make the skin younger and firmer.

WHEN USING

1. Clean and dry your face

2. Take an appropriate amount of sunscreen and apply it evenly on your face

3. Apply it before going out in the morning and use it multiple times during the day.

WARNINGS

Please keep out of reach of children. Do not swallow.Please clean your hands before use to ensure the best results from the product. Discontinue use if signs of irritation or rash occur. Store in a cool and dry place.

DO NOT USE

Discontinue use if signs of irritation or rash occur.

STOP USE

Discontinue use if signs of irritation or rash occur.

KEEP OUT OF REACH OF CHILDREN

Please keep out of reach of children. Do not swallow.

STORAGE AND HANDLING

Store in a cool and dry place.

INACTIVE INGREDIENT

AQUA、ETHYLHEXYL METHOXYCINNAMATE、ISONONYL ISONONANOATE、GLYCERYL STEARATE、TITANIUM DIOXIDE、HYALURONIC ACID、CERAMIDE NP

INDICATIONS AND USAGE

1. Clean and dry your face

2. Take an appropriate amount of sunscreen and apply it evenly on your face

3. Apply it before going out in the morning and use it multiple times during the day.

DOSAGE AND ADMINISTRATION

1. Clean and dry your face

2. Take an appropriate amount of sunscreen and apply it evenly on your face

3. Apply it before going out in the morning and use it multiple times during the day.